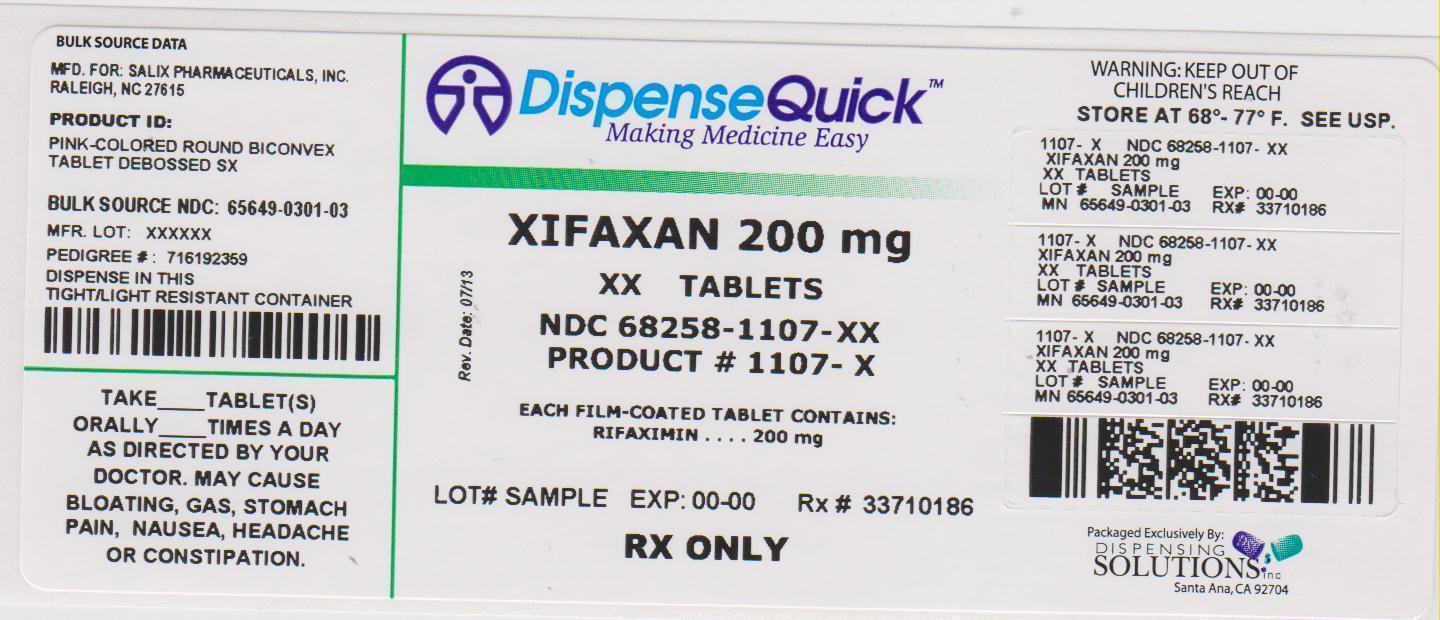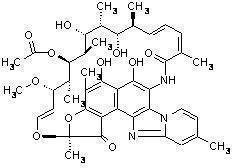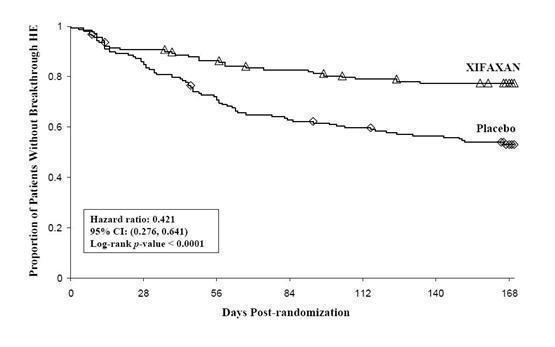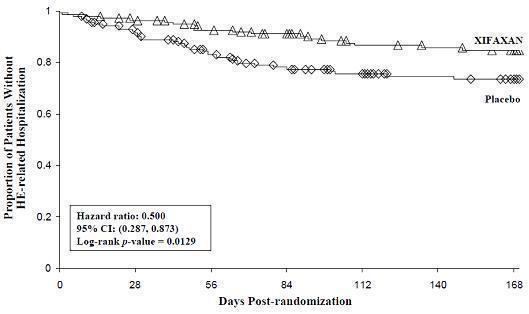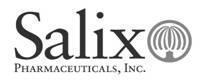 DRUG LABEL: XIFAXAN
NDC: 68258-1107 | Form: TABLET
Manufacturer: Dispensing Solutions, Inc.
Category: prescription | Type: HUMAN PRESCRIPTION DRUG LABEL
Date: 20130823

ACTIVE INGREDIENTS: RIFAXIMIN 200 mg/1 1
INACTIVE INGREDIENTS: SILICON DIOXIDE; EDETATE DISODIUM; GLYCERYL PALMITOSTEARATE; HYPROMELLOSES; CELLULOSE, MICROCRYSTALLINE; PROPYLENE GLYCOL; FERRIC OXIDE RED; SODIUM STARCH GLYCOLATE TYPE A POTATO; TALC; TITANIUM DIOXIDE

HIGHLIGHTS OF PRESCRIBING INFORMATION

These highlights do not include all the information needed to use XIFAXAN safely and effectively. See full prescribing information for XIFAXAN.
XIFAXAN® (rifaximin) Tablets
Initial U.S. Approval: 2004
To reduce the development of drug-resistant bacteria and maintain the effectiveness of XIFAXAN and other antibacterial drugs, XIFAXAN should be used only to treat or prevent infections that are proven or strongly suspected to be caused by bacteria.

1 INDICATIONS AND USAGE

XIFAXAN is a rifamycin antibacterial indicated for:

- The treatment of patients (≥ 12 years of age) with travelers’ diarrhea (TD) caused by noninvasive strains of Escherichia coli (1.1)
- Reduction in risk of overt hepatic encephalopathy (HE) recurrence in patients ≥ 18 years of age (1.2)

Limitations of Use

- TD: Do not use in patients with diarrhea complicated by fever or blood in the stool or diarrhea due to pathogens other than Escherichia coli (1.1)

2 DOSAGE AND ADMINISTRATION

- Travelers’ diarrhea: One 200 mg tablet taken orally three times a day for 3 days, with or without food (2.1)
- Hepatic encephalopathy: One 550 mg tablet taken orally two times a day, with or without food (2.2)

3 DOSAGE FORMS AND STRENGTHS

- 200 mg and 550 mg tablets (3)

4 CONTRAINDICATIONS

History of hypersensitivity to rifaximin, rifamycin antimicrobial agents, or any of the components of XIFAXAN (4.1)

5 WARNINGS AND PRECAUTIONS

- Travelers’ Diarrhea Not Caused by E. coli: XIFAXAN was not effective in diarrhea complicated by fever and/or blood in the stool or diarrhea due to pathogens other than E. coli. If diarrhea symptoms get worse or persist for more than 24-48 hours, discontinue XIFAXAN and consider alternative antibiotics (5.1)
- Clostridium difficile-Associated Diarrhea: Evaluate if diarrhea occurs after therapy or does not improve or worsens during therapy (5.2)
- Hepatic Impairment: Use with caution in patients with severe (Child-Pugh C) hepatic impairment (5.4, 8.7)

6 ADVERSE REACTIONS

- Most common adverse reactions in travelers’ diarrhea (≥ 5%): Flatulence, headache, abdominal pain, rectal tenesmus, defecation urgency and nausea (6.1)
- Most common adverse reactions in HE (≥ 10%): Peripheral edema, nausea, dizziness, fatigue, ascites, flatulence, and headache (6.1)

To report suspected adverse reactions, contact Salix Pharmaceuticals at 1-800-508-0024 and www.Salix.com or FDA at 1-800-FDA-1088 or www.fda.gov/medwatch

8 USE IN SPECIFIC POPULATIONS

- Pregnancy: Based on animal data, may cause fetal harm (8.1)
- Nursing Mothers: Discontinue nursing or drug, taking into account the importance of the drug to the mother (8.3)

FULL PRESCRIBING INFORMATION

1 INDICATIONS AND USAGE

To reduce the development of drug-resistant bacteria and maintain the effectiveness of XIFAXAN and other antibacterial drugs, XIFAXAN when used to treat infection should be used only to treat or prevent infections that are proven or strongly suspected to be caused by susceptible bacteria. When culture and susceptibility information are available, they should be considered in selecting or modifying antibacterial therapy. In the absence of such data, local epidemiology and susceptibility patterns may contribute to the empiric selection of therapy.

1.1 Travelers’ Diarrhea

XIFAXAN 200 mg is indicated for the treatment of patients (≥ 12 years of age) with travelers’ diarrhea caused by noninvasive strains of Escherichia coli [see Warningsand Precautions (5), Clinical Pharmacology (12.4) and Clinical Studies (14.1)].

Limitations of Use

XIFAXAN should not be used in patients with diarrhea complicated by fever or blood in the stool or diarrhea due to pathogens other than Escherichia coli.

1.2 Hepatic Encephalopathy

XIFAXAN 550 mg is indicated for reduction in risk of overt hepatic encephalopathy (HE) recurrence in patients ≥ 18 years of age.

In the trials of XIFAXAN for HE, 91% of the patients were using lactulose concomitantly. Differences in the treatment effect of those patients not using lactulose concomitantly could not be assessed.

XIFAXAN has not been studied in patients with MELD (Model for End-Stage Liver Disease) scores > 25, and only 8.6% of patients in the controlled trial had MELD scores over 19. There is increased systemic exposure in patients with more severe hepatic dysfunction [see Warnings and Precautions (5.4), Use in Specific Populations (8.7), Clinical Pharmacology (12.3)].

2 DOSAGE AND ADMINISTRATION

2.1 Dosage for Travelers’ Diarrhea

The recommended dose of XIFAXAN is one 200 mg tablet taken orally three times a day for 3 days. XIFAXAN can be administered orally, with or without food [see Clinical Pharmacology (12.3)].

2.2 Dosage for Hepatic Encephalopathy

The recommended dose of XIFAXAN is one 550 mg tablet taken orally two times a day, with or without food[see Clinical Pharmacology (12.3)].

3 DOSAGE FORMS AND STRENGTHS

XIFAXAN is a pink-colored biconvex tablet and is available in the following strengths:

- 200 mg – a round tablet debossed with “Sx” on one side.
- 550 mg – an oval tablet debossed with “rfx” on one side.

4 CONTRAINDICATIONS

4.1 Hypersensitivity

XIFAXAN is contraindicated in patients with a hypersensitivity to rifaximin, any of the rifamycin antimicrobial agents, or any of the components in XIFAXAN. Hypersensitivity reactions have included exfoliative dermatitis, angioneurotic edema, and anaphylaxis [see Adverse Reactions (6.2)].

5 WARNINGS AND PRECAUTIONS

5.1 Travelers’ Diarrhea Not Caused by Escherichia coli

XIFAXAN was not found to be effective in patients with diarrhea complicated by fever and/or blood in the stool or diarrhea due to pathogens other than Escherichia coli.

Discontinue XIFAXAN if diarrhea symptoms get worse or persist more than 24-48 hours and alternative antibiotic therapy should be considered.

XIFAXAN is not effective in cases of travelers’ diarrhea due to Campylobacter jejuni. The effectiveness of XIFAXAN in travelers’ diarrhea caused by Shigella spp. and Salmonella spp. has not been proven. XIFAXAN should not be used in patients where Campylobacter jejuni, Shigella spp., or Salmonella spp. may be suspected as causative pathogens.

5.2 Clostridium difficile-Associated Diarrhea

Clostridium difficile-associated diarrhea (CDAD) has been reported with use of nearly all antibacterial agents, including XIFAXAN, and may range in severity from mild diarrhea to fatal colitis. Treatment with antibacterial agents alters the normal flora of the colon which may lead to overgrowth of C. difficile.

C. difficile produces toxins A and B which contribute to the development of CDAD. Hypertoxin producing strains of C. difficile cause increased morbidity and mortality, as these infections can be refractory to antimicrobial therapy and may require colectomy. CDAD must be considered in all patients who present with diarrhea following antibiotic use. Careful medical history is necessary since CDAD has been reported to occur over two months after the administration of antibacterial agents.

If CDAD is suspected or confirmed, ongoing antibiotic use not directed against C. difficile may need to be discontinued. Appropriate fluid and electrolyte management, protein supplementation, antibiotic treatment of C. difficile, and surgical evaluation should be instituted as clinically indicated.

5.3 Development of Drug Resistant Bacteria

Prescribing XIFAXAN for travelers’ diarrhea in the absence of a proven or strongly suspected bacterial infection or a prophylactic indication is unlikely to provide benefit to the patient and increases the risk of the development of drug-resistant bacteria.

5.4 Severe (Child-Pugh C) Hepatic Impairment

There is increased systemic exposure in patients with severe hepatic impairment. Animal toxicity studies did not achieve systemic exposures that were seen in patients with severe hepatic impairment. The clinical trials were limited to patients with MELD scores <25. Therefore, caution should be exercised when administering XIFAXAN to patients with severe hepatic impairment (Child-Pugh C)

[see Use in Specific Populations (8.7), Nonclinical Toxicology (13.2) and Clinical Studies (14.2)].

6 ADVERSE REACTIONS

6.1 Clinical Studies Experience

Because clinical trials are conducted under widely varying conditions, adverse reaction rates observed in the clinical trials of a drug cannot be directly compared to rates in the clinical trials of another drug and may not reflect the rates observed in practice.

Travelers’ Diarrhea

The safety of XIFAXAN 200 mg taken three times a day was evaluated in patients with travelers’ diarrhea consisting of 320 patients in two placebo-controlled clinical trials with 95% of patients receiving three or four days of treatment with XIFAXAN. The population studied had a mean age of 31.3 (18-79) years of which approximately 3% were ≥ 65 years old, 53% were male and 84% were White, 11% were Hispanic.

Discontinuations due to adverse reactions occurred in 0.4% of patients. The adverse reactions leading to discontinuation were taste loss, dysentery, weight decrease, anorexia, nausea and nasal passage irritation.

All adverse reactions for XIFAXAN 200 mg three times daily that occurred at a frequency ≥ 2% in the two placebo-controlled trials combined are provided in Table 1. (These include adverse reactions that may be attributable to the underlying disease.)

Table 1. All Adverse Reactions With an Incidence ≥2% Among Patients Receiving XIFAXAN Tablets, 200 mg Three Times Daily, in Placebo-Controlled Studies
MedDRA Preferred Term | Number (%) of Patients
MedDRA Preferred Term | XIFAXAN Tablets, 600 mg/day (N = 320) | Placebo N = 228
Flatulence | 36 (11%) | 45 (20%)
Headache | 31 (10%) | 21 (9%)
Abdominal Pain NOS* | 23 (7%) | 23 (10%)
Rectal Tenesmus | 23 (7%) | 20 (9%)
Defecation Urgency | 19 (6%) | 21 (9%)
Nausea | 17 (5%) | 19 (8%)
Constipation | 12 (4%) | 8 (4%)
Pyrexia | 10 (3%) | 10 (4%)
Vomiting NOS | 7 (2%) | 4 (2%)
*NOS: Not otherwise specified

The following adverse reactions, presented by body system, have also been reported in <2% of patients taking XIFAXAN in the two placebo-controlled clinical trials where the 200 mg tablet was taken three times a day for travelers’ diarrhea. The following includes adverse reactions regardless of causal relationship to drug exposure.

Blood and Lymphatic System Disorders: Lymphocytosis, monocytosis, neutropenia

Ear and Labyrinth Disorders: Ear pain, motion sickness, tinnitus

Gastrointestinal Disorders: Abdominal distension, diarrhea NOS, dry throat, fecal abnormality NOS, gingival disorder NOS, inguinal hernia NOS, dry lips, stomach discomfort

General Disorders and Administration Site Conditions: Chest pain, fatigue, malaise, pain NOS, weakness

Infections and Infestations: Dysentery NOS, respiratory tract infection NOS, upper respiratory tract infection NOS

Injury and Poisoning: Sunburn

Investigations: Aspartate aminotransferase increased, blood in stool, blood in urine, weight decreased

Metabolic and Nutritional Disorders: Anorexia, dehydration

Musculoskeletal, Connective Tissue, and Bone Disorders: Arthralgia, muscle spasms, myalgia, neck pain

Nervous System Disorders: Abnormal dreams, dizziness, migraine NOS, syncope, loss of taste

Psychiatric Disorders: Insomnia

Renal and Urinary Disorders: Choluria, dysuria, hematuria, polyuria, proteinuria, urinary frequency

Respiratory, Thoracic, and Mediastinal Disorders: Dyspnea NOS, nasal passage irritation, nasopharyngitis, pharyngitis, pharyngolaryngeal pain, rhinitis NOS, rhinorrhea

Skin and Subcutaneous Tissue Disorders: Clamminess, rash NOS, sweating increased

Vascular Disorders: Hot flashes NOS

Hepatic Encephalopathy

The data described below reflect exposure to XIFAXAN 550 mg in 348 patients, including 265 exposed for 6 months and 202 exposed for more than a year (mean exposure was 364 days). The safety of XIFAXAN 550 mg taken two times a day for reducing the risk of overt hepatic encephalopathy recurrence in adult patients was evaluated in a 6-month placebo-controlled clinical trial (n = 140) and in a long term follow-up study (n = 280). The population studied had a mean age of 56.26 (range: 21-82) years; approximately 20% of the patients were ≥ 65 years old, 61% were male, 86% were White, and 4% were Black. Ninety-one percent of patients in the trial were taking lactulose concomitantly. All adverse reactions that occurred at an incidence ≥ 5% and at a higher incidence in XIFAXAN 550 mg-treated subjects than in the placebo group in the 6-month trial are provided in Table 2. (These include adverse events that may be attributable to the underlying disease).

Table 2: Adverse Reactions Occurring in ≥ 5% of Patients Receiving XIFAXAN and at a Higher Incidence Than Placebo
 | Number (%) of Patients
MedDRA Preferred Term | XIFAXAN Tablets 550 mg TWICE DAILY N = 140 | Placebo N = 159
MedDRA Preferred Term | Edema peripheral | 21 (15%) | 13 (8%)
Nausea | 20 (14%) | 21 (13%)
Dizziness | 18 (13%) | 13 (8%)
Fatigue | 17 (12%) | 18 (11%)
Ascites | 16 (11%) | 15 (9%)
Muscle spasms | 13 (9%) | 11 (7%)
Pruritus | 13 (9%) | 10 (6%)
Abdominal pain | 12 (9%) | 13 (8%)
Abdominal distension | 11 (8%) | 12 (8%)
Anemia | 11 (8%) | 6 (4%)
Cough | 10 (7%) | 11 (7%)
Depression | 10 (7%) | 8 (5%)
Insomnia | 10 (7%) | 11 (7%)
Nasopharyngitis | 10 (7%) | 10 (6%)
Abdominal pain upper | 9 (6%) | 8 (5%)
Arthralgia | 9 (6%) | 4 (3%)
Back pain | 9 (6%) | 10 (6%)
Constipation | 9 (6%) | 10 (6%)
Dyspnea | 9 (6%) | 7 (4%)
Pyrexia | 9 (6%) | 5 (3%)
Rash | 7 (5%) | 6 (4%)

The following adverse reactions, presented by body system, have also been reported in the placebo-controlled clinical trial in greater than 2% but less than 5% of patients taking XIFAXAN 550 mg taken orally two times a day for hepatic encephalopathy. The following includes adverse events occurring at a greater incidence than placebo, regardless of causal relationship to drug exposure.

Ear and Labyrinth Disorders: Vertigo

Gastrointestinal Disorders: Abdominal pain lower, abdominal tenderness, dry mouth, esophageal variceal bleed, stomach discomfort

General Disorders and Administration Site Conditions: Chest pain, generalized edema, influenza like illness, pain NOS

Infections and Infestations: Cellulitis, pneumonia, rhinitis, upper respiratory tract infection NOS

Injury, Poisoning and Procedural Complications: Contusion, fall, procedural pain

Investigations: Weight increased

Metabolic and Nutritional Disorders: Anorexia, dehydration, hyperglycemia, hyperkalemia, hypoglycemia, hyponatremia

Musculoskeletal, Connective Tissue, and Bone Disorders: Myalgia, pain in extremity

Nervous System Disorders: Amnesia, disturbance in attention, hypoesthesia, memory impairment, tremor

Psychiatric Disorders: Confusional state

Respiratory, Thoracic, and Mediastinal Disorders: Epistaxis

Vascular Disorders: Hypotension

6.2 Postmarketing Experience

The following adverse reactions have been identified during post approval use of XIFAXAN. Because these reactions are reported voluntarily from a population of unknown size, estimates of frequency cannot be made. These reactions have been chosen for inclusion due to either their seriousness, frequency of reporting or causal connection to XIFAXAN.

Infections and Infestations

Cases of C. difficile-associated colitis have been reported [see Warnings and Precautions (5.2)].

General

Hypersensitivity reactions, including exfoliative dermatitis, rash, angioneurotic edema (swelling of face and tongue and difficulty swallowing), urticaria, flushing, pruritus and anaphylaxis have been reported. These events occurred as early as within 15 minutes of drug administration.

7 DRUG INTERACTIONS

In vitro studies have shown that rifaximin did not inhibit cytochrome P450 isoenzymes 1A2, 2A6, 2B6, 2C9, 2C19, 2D6, 2E1 and CYP3A4 at concentrations ranging from 2 to 200 ng/mL [see Clinical Pharmacology (12.3)]. Rifaximin is not expected to inhibit these enzymes in clinical use.

An in vitro study has suggested that rifaximin induces CYP3A4 [see Clinical Pharmacology (12.3)]. However, in patients with normal liver function, rifaximin at the recommended dosing regimen is not expected to induce CYP3A4. It is unknown whether rifaximin can have a significant effect on the pharmacokinetics of concomitant CYP3A4 substrates in patients with reduced liver function who have elevated rifaximin concentrations.

An in vitro study suggested that rifaximin is a substrate of P-glycoprotein. It is unknown whether concomitant drugs that inhibit P-glycoprotein can increase the systemic exposure of rifaximin [see Clinical Pharmacology (12.3)].

8 USE IN SPECIFIC POPULATIONS

8.1 Pregnancy

Pregnancy Category C

There are no adequate and well controlled studies in pregnant women. Rifaximin has been shown to be teratogenic in rats and rabbits at doses that caused maternal toxicity. XIFAXAN tablets should be used during pregnancy only if the potential benefit justifies the potential risk to the fetus.

Administration of rifaximin to pregnant rats and rabbits at dose levels that caused reduced body weight gain resulted in eye malformations in both rat and rabbit fetuses. Additional malformations were observed in fetal rabbits that included cleft palate, lumbar scoliosis, brachygnathia, interventricular septal defect, and large atrium.

The fetal rat malformations were observed in a study of pregnant rats administered a high dose that resulted in 16 times the therapeutic dose to diarrheic patients or 1 times the therapeutic dose to patients with hepatic encephalopathy (based upon plasma AUC comparisons). Fetal rabbit malformations were observed from pregnant rabbits administered mid and high doses that resulted in 1 or 2 times the therapeutic dose to diarrheic patients or less than 0.1 times the dose in patients with hepatic encephalopathy, based upon plasma AUC comparisons.

Post-natal developmental effects were not observed in rat pups from pregnant/lactating female rats dosed during the period from gestation to Day 20 post-partum at the highest dose which resulted in approximately 16 times the human therapeutic dose for travelers’ diarrhea (based upon AUCs) or approximately 1 times the AUCs derived from therapeutic doses to patients with hepatic encephalopathy.

8.3 Nursing Mothers

It is not known whether rifaximin is excreted in human milk. Because many drugs are excreted in human milk and because of the potential for adverse reactions in nursing infants from XIFAXAN, a decision should be made whether to discontinue nursing or to discontinue the drug, taking into account the importance of the drug to the mother.

8.4 Pediatric Use

The safety and effectiveness of XIFAXAN 200 mg in pediatric patients with travelers’ diarrhea less than 12 years of age have not been established.

The safety and effectiveness of XIFAXAN 550 mg for HE have not been established in patients < 18 years of age.

8.5 Geriatric Use

Clinical studies with rifaximin 200 mg for travelers’ diarrhea did not include sufficient numbers of patients aged 65 and over to determine whether they respond differently than younger subjects.

In the controlled trial with XIFAXAN 550 mg for hepatic encephalopathy, 19.4% were 65 and over, while 2.3% were 75 and over. No overall differences in safety or effectiveness were observed between these subjects and younger subjects, and other reported clinical experience has not identified differences in responses between the elderly and younger patients, but greater sensitivity of some older individuals cannot be ruled out.

8.6 Renal Impairment

The pharmacokinetics of rifaximin in patients with impaired renal function has not been studied.

8.7 Hepatic Impairment

Following administration of XIFAXAN 550 mg twice daily to patients with a history of hepatic encephalopathy, the systemic exposure (i.e., AUCτ) of rifaximin was about 10-, 13-, and 20-fold higher in those patients with mild (Child-Pugh A), moderate (Child-Pugh B) and severe (Child-Pugh C) hepatic impairment, respectively, compared to that in healthy volunteers. No dosage adjustment is recommended because rifaximin is presumably acting locally. Nonetheless, caution should be exercised when XIFAXAN is administered to patients with severe hepatic impairment

[see Warnings and Precautions (5.4), Clinical Pharmacology (12.3), Nonclinical Toxicology (13.2), and Clinical Studies (14.2)].

10 OVERDOSAGE

No specific information is available on the treatment of overdosage with XIFAXAN. In clinical studies at doses higher than the recommended dose (> 600 mg/day for travelers’ diarrhea or > 1100 mg/day for hepatic encephalopathy), adverse reactions were similar in subjects who received doses higher than the recommended dose and placebo. In the case of overdosage, discontinue XIFAXAN, treat symptomatically, and institute supportive measures as required.

11 DESCRIPTION

XIFAXAN tablets contain rifaximin, a non-aminoglycoside semi-synthetic, nonsystemic antibiotic derived from rifamycin SV. Rifaximin is a structural analog of rifampin. The chemical name for rifaximin is (2S,16Z,18E,20S,21S,22R,23R,24R,25S,26S,27S,28E)-5,6,21,23,25-pentahydroxy-27-methoxy-2,4,11,16,20,22,24,26-octamethyl-2,7-(epoxypentadeca-[1,11,13]trienimino)benzofuro[4,5-e]pyrido[1,2-á]-benzimidazole-1,15(2H)-dione,25-acetate. The empirical formula is C43H51N3O11 and its molecular weight is 785.9. The chemical structure is represented below:

XIFAXAN Tablets for oral administration are film-coated and contain 200 mg or 550 mg of rifaximin.

Inactive ingredients:

Each 200 mg tablet contains colloidal silicon dioxide, disodium edetate, glycerol palmitostearate, hypromellose, microcrystalline cellulose, propylene glycol, red iron oxide, sodium starch glycolate, talc, and titanium dioxide.

Each 550 mg tablet contains colloidal silicon dioxide, glycerol palmitostearate, microcrystalline cellulose, polyethylene glycol/macrogol, polyvinyl alcohol, red iron oxide, sodium starch glycolate, talc, and titanium dioxide.

12 CLINICAL PHARMACOLOGY

12.1 Mechanism of Action

Rifaximin is an antibacterial drug [see Clinical Pharmacology (12.4)].

12.3 Pharmacokinetics

Absorption

Travelers’ Diarrhea

Systemic absorption of rifaximin (200 mg three times daily) was evaluated in 13 subjects challenged with shigellosis on Days 1 and 3 of a three-day course of treatment. Rifaximin plasma concentrations and exposures were low and variable. There was no evidence of accumulation of rifaximin following repeated administration for 3 days (9 doses). Peak plasma rifaximin concentrations after 3 and 9 consecutive doses ranged from 0.81 to 3.4 ng/mL on Day 1 and 0.68 to 2.26 ng/mL on Day 3. Similarly, AUC0-last estimates were 6.95 ± 5.15 ng•h/mL on Day 1 and 7.83 ± 4.94 ng•h/mL on Day 3. XIFAXAN is not suitable for treating systemic bacterial infections because of limited systemic exposure after oral administration [see Warnings and Precautions (5.1)].

Hepatic Encephalopathy

After a single dose and multiple doses of rifaximin 550 mg in healthy subjects, the mean time to reach peak plasma concentrations was about an hour. The pharmacokinetic (PK) parameters were highly variable and the accumulation ratio based on AUC was 1.37.

The PK of rifaximin in patients with a history of HE was evaluated after administration of XIFAXAN, 550 mg two times a day. The PK parameters were associated with a high variability and mean rifaximin exposure (AUCτ) in patients with a history of HE (147 ng•h/mL) was approximately 12-fold higher than that observed in healthy subjects following the same dosing regimen (12.3 ng•h/mL). When PK parameters were analyzed based on Child-Pugh Class A, B, and C, the mean AUCτ was 10-, 13-, and 20-fold higher, respectively, compared to that in healthy subjects (Table 3).

Table 3. Mean (± SD) Pharmacokinetic Parameters of Rifaximin at Steady-State in Patients with a History of Hepatic Encephalopathy by Child-Pugh Class^1
 | Healthy Subjects (n = 14) | Child-Pugh Class
 | Healthy Subjects (n = 14) | A (n = 18) | B (n = 7) | C (n = 4)
AUCtau; (ng•h/mL) | 12.3 ± 4.8 | 118 ± 67.8 | 161 ± 101 | 246 ± 120
Cmax; (ng/mL) | 3.4 ± 1.6 | 19.5 ± 11.4 | 25.1 ± 12.6 | 35.5 ± 12.5
Tmax^2; (h) | 0.8 (0.5, 4.0) | 1 (0.9, 10) | 1 (0.97, 1) | 1 (0, 2)
^1Cross-study comparison with PK parameters in healthy subjects
^2Median (range)

Food Effect in Healthy Subjects

A high-fat meal consumed 30 minutes prior to XIFAXAN dosing in healthy subjects delayed the mean time to peak plasma concentration from 0.75 to 1.5 hours and increased the systemic exposure (AUC) of rifaximin by 2-fold (Table 4).

Table 4. Mean (± SD) Pharmacokinetic Parameters After Single-Dose Administration of XIFAXAN Tablets 550 mg in Healthy Subjects Under Fasting and Fed Conditions (N = 12)
Parameter | Fasting | Fed
Cmax (ng/mL) | 4.1 ± 1.5 | 4.8 ± 4.3
Tmax^1 (h) | 0.8 (0.5, 2.1) | 1.5 (0.5, 4.1)
Half-Life (h) | 1.8 ± 1.4 | 4.8 ± 1.3
AUC (ng•h/mL) | 11.1 ± 4.2 | 22.5 ± 12
^1 Median (range)

XIFAXAN can be administered with or without food [see Dosage and Administration (2.1 and 2.2)].

Distribution

Rifaximin is moderately bound to human plasma proteins. In vivo, the mean protein binding ratio was 67.5% in healthy subjects and 62% in patients with hepatic impairment when XIFAXAN 550 mg was administered.

Metabolism and Excretion

In a mass balance study, after administration of 400 mg ^14C-rifaximin orally to healthy volunteers, of the 96.94% total recovery, 96.62% of the administered radioactivity was recovered in feces almost exclusively as the unchanged drug and 0.32% was recovered in urine mostly as metabolites with 0.03% as the unchanged drug. Rifaximin accounted for 18% of radioactivity in plasma. This suggests that the absorbed rifaximin undergoes metabolism with minimal renal excretion of the unchanged drug. The enzymes responsible for metabolizing rifaximin are unknown.

In a separate study, rifaximin was detected in the bile after cholecystectomy in patients with intact gastrointestinal mucosa, suggesting biliary excretion of rifaximin.

Specific Populations

Hepatic Impairment

The systemic exposure of rifaximin was markedly elevated in patients with hepatic impairment compared to healthy subjects. The mean AUC in patients with Child-Pugh Class C hepatic impairment was 2-fold higher than in patients with Child-Pugh Class A hepatic impairment (see Table 3), [see Warnings and Precautions (5.4) and Use in Specific Populations (8.7)].

Renal Impairment

The pharmacokinetics of rifaximin in patients with impaired renal function has not been studied.

Drug Interactions

In vitro drug interaction studies have shown that rifaximin, at concentrations ranging from 2 to 200 ng/mL, did not inhibit human hepatic cytochrome P450 isoenzymes 1A2, 2A6, 2B6, 2C9, 2C19, 2D6, 2E1, and 3A4.

In an in vitro study, rifaximin was shown to induce CYP3A4 at the concentration of 0.2 µM.

An in vitro study suggests that rifaximin is a substrate of P-glycoprotein. In the presence of P-glycoprotein inhibitor verapamil, the efflux ratio of rifaximin was reduced greater than 50% in vitro. The effect of P-glycoprotein inhibition on rifaximin was not evaluated in vivo.

The inhibitory effect of rifaximin on P-gp transporter was observed in an in vitro study. The effect of rifaximin on P-gp transporter was not evaluated in vivo.

Midazolam

The effect of rifaximin 200 mg administered orally every 8 hours for 3 days and for 7 days on the pharmacokinetics of a single dose of either midazolam 2 mg intravenous or midazolam 6 mg orally was evaluated in healthy subjects. No significant difference was observed in the metrics of systemic exposure or elimination of intravenous or oral midazolam or its major metabolite, 1’-hydroxymidazolam, between midazolam alone or together with rifaximin. Therefore, rifaximin was not shown to significantly affect intestinal or hepatic CYP3A4 activity for the 200 mg three times a day dosing regimen.

After XIFAXAN 550 mg was administered three times a day for 7 days and 14 days to healthy subjects, the mean AUC of single midazolam 2 mg orally was 3.8% and 8.8% lower, respectively, than when midazolam was administered alone. The mean Cmax of midazolam was also decreased by 4-5% when XIFAXAN was administered for 7-14 days prior to midazolam administration. This degree of interaction is not considered clinically meaningful.

The effect of rifaximin on CYP3A4 in patients with impaired liver function who have elevated systemic exposure is not known.

Oral Contraceptives Containing 0.07 mg Ethinyl Estradiol and 0.5 mg Norgestimate

The oral contraceptive study utilized an open-label, crossover design in 28 healthy female subjects to determine if rifaximin 200 mg orally administered three times a day for 3 days (the dosing regimen for travelers’ diarrhea) altered the pharmacokinetics of a single dose of an oral contraceptive containing 0.07 mg ethinyl estradiol and 0.5 mg norgestimate. Results showed that the pharmacokinetics of single doses of ethinyl estradiol and norgestimate were not altered by rifaximin [see Drug Interactions (7)].

Effect of rifaximin on oral contraceptives was not studied for XIFAXAN 550 mg twice a day, the dosing regimen for hepatic encephalopathy.

12.4 Microbiology

Mechanism of Action

Rifaximin is a non-aminoglycoside semi-synthetic antibacterial derived from rifamycin SV. Rifaximin acts by binding to the beta-subunit of bacterial DNA-dependent RNA polymerase resulting in inhibition of bacterial RNA synthesis.

Escherichia coli has been shown to develop resistance to rifaximin in vitro. However, the clinical significance of such an effect has not been studied.

Rifaximin is a structural analog of rifampin. Organisms with high rifaximin minimum inhibitory concentration (MIC) values also have elevated MIC values against rifampin. Cross-resistance between rifaximin and other classes of antimicrobials has not been studied.

Rifaximin has been shown to be active against the following pathogen in clinical studies of infectious diarrhea as described in the Indications and Usage (1) section: Escherichia coli (enterotoxigenic and enteroaggregative strains).

For HE, rifaximin is thought to have an effect on the gastrointestinal flora.

Susceptibility Tests

In vitro susceptibility testing was performed according to the National Committee for Clinical Laboratory Standards (NCCLS) agar dilution method M7-A6 [see References (15)]. However, the correlation between susceptibility testing and clinical outcome has not been determined.

13 NONCLINICAL TOXICOLOGY

13.1 Carcinogenesis, Mutagenesis, Impairment of Fertility

Malignant schwannomas in the heart were significantly increased in male Crl:CD® (SD) rats that received rifaximin by oral gavage for two years at 150 to 250 mg/kg/day (doses equivalent to 2.4 to 4 times the recommended dose of 200 mg three times daily for travelers’ diarrhea, and equivalent to 1.3 to 2.2 times the recommended dose of 550 mg twice daily for hepatic encephalopathy, based on relative body surface area comparisons). There was no increase in tumors in Tg.rasH2 mice dosed orally with rifaximin for 26 weeks at 150 to 2000 mg/kg/day (doses equivalent to 1.2 to 16 times the recommended daily dose for travelers’ diarrhea and equivalent to 0.7 to 9 times the recommended daily dose for hepatic encephalopathy, based on relative body surface area comparisons).

Rifaximin was not genotoxic in the bacterial reverse mutation assay, chromosomal aberration assay, rat bone marrow micronucleus assay, rat hepatocyte unscheduled DNA synthesis assay, or the CHO/HGPRT mutation assay. There was no effect on fertility in male or female rats following the administration of rifaximin at doses up to 300 mg/kg (approximately 5 times the clinical dose of 600 mg/day, and approximately 2.6 times the clinical dose of 1100 mg/day, adjusted for body surface area).

13.2 Animal Toxicology and/or Pharmacology

Oral administration of rifaximin for 3-6 months produced hepatic proliferation of connective tissue in rats (50 mg/kg/day) and fatty degeneration of liver in dogs (100 mg/kg/day). However, plasma drug levels were not measured in these studies. Subsequently, rifaximin was studied at doses as high as 300 mg/kg/day in rats for 6 months and 1000 mg/kg/day in dogs for 9 months, and no signs of hepatotoxicity were observed. The maximum plasma AUC0-8 hr values from the 6 month rat and 9 month dog toxicity studies (range: 42-127 ng•h/mL) was lower than the maximum plasma AUC0-8 hr values in cirrhotic patients (range: 19-306 ng•h/mL).

14 CLINICAL STUDIES

14.1 Travelers’ Diarrhea

The efficacy of XIFAXAN given as 200 mg orally taken three times a day for 3 days was evaluated in 2 randomized, multi‑center, double-blind, placebo-controlled studies in adult subjects with travelers’ diarrhea. One study was conducted at clinical sites in Mexico, Guatemala, and Kenya (Study 1). The other study was conducted in Mexico, Guatemala, Peru, and India (Study 2). Stool specimens were collected before treatment and 1 to 3 days following the end of treatment to identify enteric pathogens. The predominant pathogen in both studies was Escherichia coli.

The clinical efficacy of XIFAXAN was assessed by the time to return to normal, formed stools and resolution of symptoms. The primary efficacy endpoint was time to last unformed stool (TLUS) which was defined as the time to the last unformed stool passed, after which clinical cure was declared. Table 5 displays the median TLUS and the number of patients who achieved clinical cure for the intent to treat (ITT) population of Study 1. The duration of diarrhea was significantly shorter in patients treated with XIFAXAN than in the placebo group. More patients treated with XIFAXAN were classified as clinical cures than were those in the placebo group.

Table 5. Clinical Response in Study 1 (ITT population)
 | XIFAXAN (n=125) | Placebo (n=129) | Estimate (97.5% CI) | P-Value
Median TLUS (hours) | 32.5 | 58.6 | 1.78a; (1.26, 2.50) | 0.0002
Clinical cure, n (%) | 99 (79.2) | 78 (60.5) | 18.7b (5.3, 32.1) | 0.001
a Hazard Ratio
b Difference in rates

Microbiological eradication (defined as the absence of a baseline pathogen in culture of stool after 72 hours of therapy) rates for Study 1 are presented in Table 6 for patients with any pathogen at baseline and for the subset of patients with Escherichia coli at baseline. Escherichia coli was the only pathogen with sufficient numbers to allow comparisons between treatment groups.

Even though XIFAXAN had microbiologic activity similar to placebo, it demonstrated a clinically significant reduction in duration of diarrhea and a higher clinical cure rate than placebo. Therefore, patients should be managed based on clinical response to therapy rather than microbiologic response.

Table 6. Microbiologic Eradication Rates in Study 1 Subjects with a Baseline Pathogen
 | XIFAXAN | Placebo
Overall | 48/70 (68.6) | 41/61 (67.2)
E. coli | 38/53 (71.7) | 40/54 (74.1)

The results of Study 2 supported the results presented for Study 1. In addition, this study provided evidence that subjects treated with XIFAXAN with fever and/or blood in the stool at baseline had prolonged TLUS. These subjects had lower clinical cure rates than those without fever or blood in the stool at baseline. Many of the patients with fever and/or blood in the stool (dysentery-like diarrheal syndromes) had invasive pathogens, primarily Campylobacter jejuni, isolated in the baseline stool.

Also in this study, the majority of the subjects treated with XIFAXAN who had Campylobacter jejuni isolated as a sole pathogen at baseline failed treatment and the resulting clinical cure rate for these patients was 23.5% (4/17). In addition to not being different from placebo, the microbiologic eradication rates for subjects with Campylobacter jejuni isolated at baseline were much lower than the eradication rates seen for Escherichia coli.

In an unrelated open-label, pharmacokinetic study of oral XIFAXAN 200 mg taken every 8 hours for 3 days, 15 adult subjects were challenged with Shigella flexneri 2a, of whom 13 developed diarrhea or dysentery and were treated with XIFAXAN. Although this open-label challenge trial was not adequate to assess the effectiveness of XIFAXAN in the treatment of shigellosis, the following observations were noted: eight subjects received rescue treatment with ciprofloxacin either because of lack of response to XIFAXAN treatment within 24 hours (2), or because they developed severe dysentery (5), or because of recurrence of Shigella flexneri in the stool (1); five of the 13 subjects received ciprofloxacin although they did not have evidence of severe disease or relapse.

14.2 Hepatic Encephalopathy

The efficacy of XIFAXAN 550 mg taken orally two times a day was evaluated in a randomized, placebo-controlled, double-blind, multi-center 6-month trial of adult subjects from the U.S., Canada and Russia who were defined as being in remission (Conn score of 0 or 1) from hepatic encephalopathy (HE). Eligible subjects had ≥ 2 episodes of HE associated with chronic liver disease in the previous 6 months.

A total of 299 subjects were randomized to receive either XIFAXAN (n=140) or placebo (n=159) in this study. Patients had a mean age of 56 years (range, 21-82 years), 81% < 65 years of age, 61% were male and 86% White. At baseline, 67% of patients had a Conn score of 0 and 68% had an asterixis grade of 0. Patients had MELD scores of either ≤ 10 (27%) or 11 to 18 (64%) at baseline. No patients were enrolled with a MELD score of > 25. Nine percent of the patients were Child-Pugh Class C. Lactulose was concomitantly used by 91% of the patients in each treatment arm of the study. Per the study protocol, patients were withdrawn from the study after experiencing a breakthrough HE episode. Other reasons for early study discontinuation included: adverse reactions (XIFAXAN 6%; placebo 4%), patient request to withdraw (XIFAXAN 4%; placebo 6%) and other (XIFAXAN 7%; placebo 5%).

The primary endpoint was the time to first breakthrough overt HE episode. A breakthrough overt HE episode was defined as a marked deterioration in neurological function and an increase of Conn score to Grade ≥ 2. In patients with a baseline Conn score of 0, a breakthrough overt HE episode was defined as an increase in Conn score of 1 and asterixis grade of 1.

Breakthrough overt HE episodes were experienced by 31 of 140 subjects (22%) in the XIFAXAN group and by 73 of 159 subjects (46%) in the placebo group during the 6-month treatment period. Comparison of Kaplan-Meier estimates of event-free curves showed XIFAXAN significantly reduced the risk of HE breakthrough by 58% during the 6-month treatment period. Presented below in Figure 1 is the Kaplan-Meier event-free curve for all subjects (n = 299) in the study.

Figure 1: Kaplan-Meier Event-Free Curves^1 in HE Study (Time to First
Breakthrough-HE Episode up to 6 Months of Treatment, Day 170) (ITT
Population)

Note: Open diamonds and open triangles represent censored subjects.
^1Event-free refers to non-occurrence of breakthrough HE.

When the results were evaluated by the following demographic and baseline characteristics, the treatment effect of XIFAXAN 550 mg in reducing the risk of breakthrough overt HE recurrence was consistent for: sex, baseline Conn score, duration of current remission and diabetes. The differences in treatment effect could not be assessed in the following subpopulations due to small sample size: non-White (n=42), baseline MELD > 19 (n=26), Child-Pugh C (n=31), and those without concomitant lactulose use (n=26).

HE-related hospitalizations (hospitalizations directly resulting from HE, or hospitalizations complicated by HE) were reported for 19 of 140 subjects (14%) and 36 of 159 subjects (23%) in the XIFAXAN and placebo groups respectively. Comparison of Kaplan-Meier estimates of event-free curves showed XIFAXAN significantly reduced the risk of HE-related hospitalizations by 50% during the 6-month treatment period. Comparison of Kaplan-Meier estimates of event-free curves is shown in Figure 2.

Figure 2: Kaplan-Meier Event-Free Curves^1 in Pivotal HE Study (Time
to First HE-Related Hospitalization in HE Study up to 6 Months of
Treatment, Day 170) (ITT Population)

Note: Open diamonds and open triangles represent censored subjects.
^1Event-free refers to non-occurrence of HE-related hospitalization.

15 REFERENCES

Methods for dilution antimicrobial susceptibility tests for bacteria that grow aerobically. National Committee for Clinical Laboratory Standards, Sixth Edition, Wayne PA. Approved Standard NCCLS Document M7-A6 January 2003; 23 (2).

16 HOW SUPPLIED/STORAGE AND HANDLING

HOW SUPPLIED

200 mg tablet is a pink-colored, round, biconvex tablet with “Sx” debossed on one side. It is available in the following presentations:

- NDC 65649-301-03, bottles of 30 tablets
- NDC 65649-301-41, bottles of 100 tablets
- NDC 65649-301-05, carton of 100 tablets, unit dose

The 550 mg tablet is a pink-colored, oval, biconvex tablet with “rfx” debossed on one side. It is available in the following presentations:

- NDC 65649-303-02, bottles of 60 tablets
- NDC 65649-303-03, carton of 60 tablets, unit dose

Storage

Store XIFAXAN Tablets at 20–25°C (68–77°F); excursions permitted to 15–30°C (59-86°F). See USP Controlled Room Temperature.

17 PATIENT COUNSELING INFORMATION

17.1 Persistent Diarrhea

For those patients being treated for travelers’ diarrhea, discontinue XIFAXAN if diarrhea persists more than 24-48 hours or worsens. Advise the patient to seek medical care for fever and/or blood in the stool [see Warnings and Precautions (5.1)].

17.2 Clostridium difficile-Associated Diarrhea

Clostridium difficile-associated diarrhea (CDAD) has been reported with use of nearly all antibacterial agents, including XIFAXAN, and may range in severity from mild diarrhea to fatal colitis. Treatment with antibiotics alters the normal flora of the colon which may lead to C. difficile. Patients can develop watery and bloody stools (with or without stomach cramps and fever) even as late as two or more months after having taken the last dose of the antibiotic. If diarrhea occurs after therapy or does not improve or worsens during therapy, advise patients to contact a physician as soon as possible [see Warnings and Precautions (5.4)].

17.3 Administration with Food

Inform patients that XIFAXAN may be taken with or without food.

17.4 Antibacterial Resistance

Counsel patients that antibacterial drugs including XIFAXAN should only be used to treat bacterial infections. They do not treat viral infections (e.g., the common cold). When XIFAXAN is prescribed to treat a bacterial infection, patients should be told that although it is common to feel better early in the course of therapy, the medication should be taken exactly as directed. Skipping doses or not completing the full course of therapy may (1) decrease the effectiveness of the immediate treatment and (2) increase the likelihood that bacteria will develop resistance and will not be treatable by XIFAXAN or other antibacterial drugs in the future.

17.5 Severe Hepatic Impairment

Patients should be informed that in patients with severe hepatic impairment (Child-Pugh C) there is an increase in systemic exposure to XIFAXAN [see Warnings and Precautions (5.4)].

Manufactured for:

Salix Pharmaceuticals, Inc.

Raleigh, NC 27615

XIFAXAN® is a trademark of Salix Pharmaceuticals, Inc., under license from Alfa Wassermann S.p.A.
Copyright © Salix Pharmaceuticals, Inc.

Rifaximin for Travelers' Diarrhea and Hepatic encephalopathy is protected by US Patent Nos. 7,045,620; 7,612,199; 7,902,206 and 7,906,542. Rifaximin for Travelers' Diarrhea is also protected by US Patent No. 7,928,115.

Web site: www.Salix.com

All rights reserved.

VENART-156-2

OCT 2011

PACKAGE LABEL - PRINCIPAL DISPLAY

NDC 68258-1107-XX

NDC 68258-1107-01

NDC 68258-1107-02

NDC 68258-1107-04